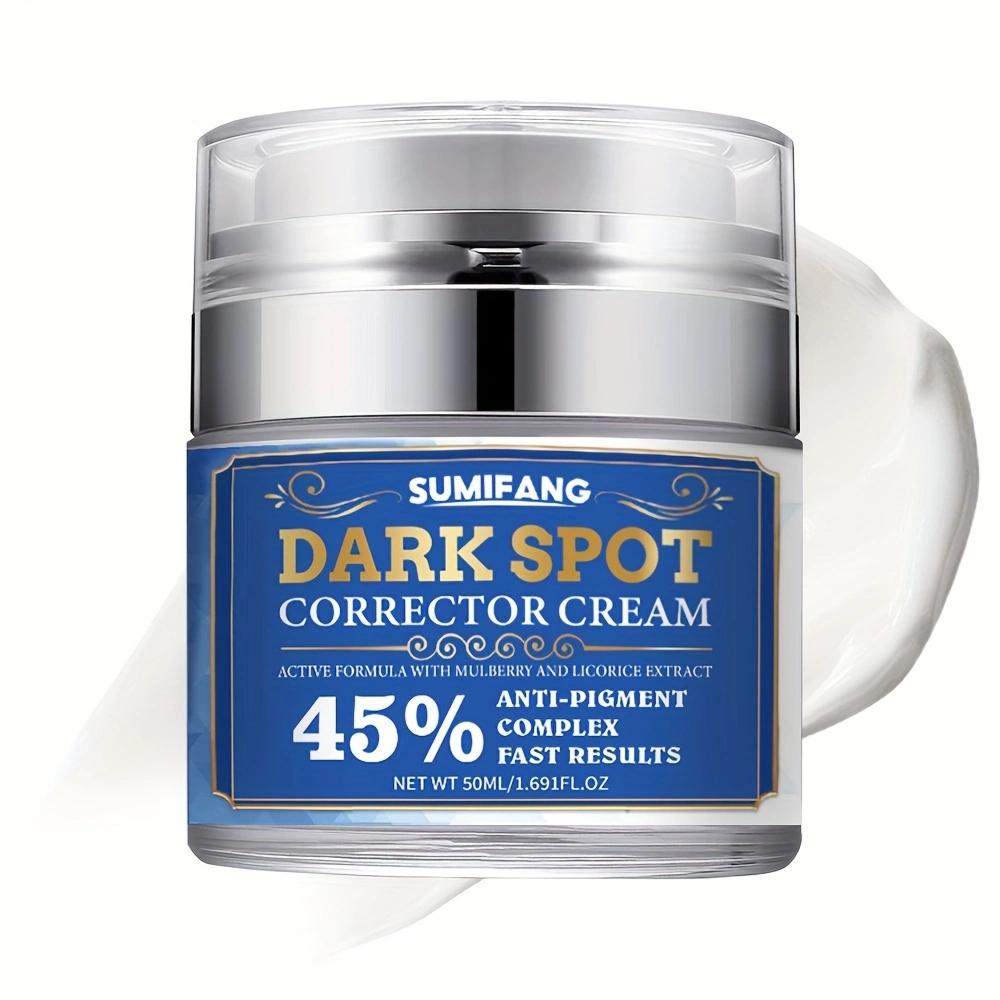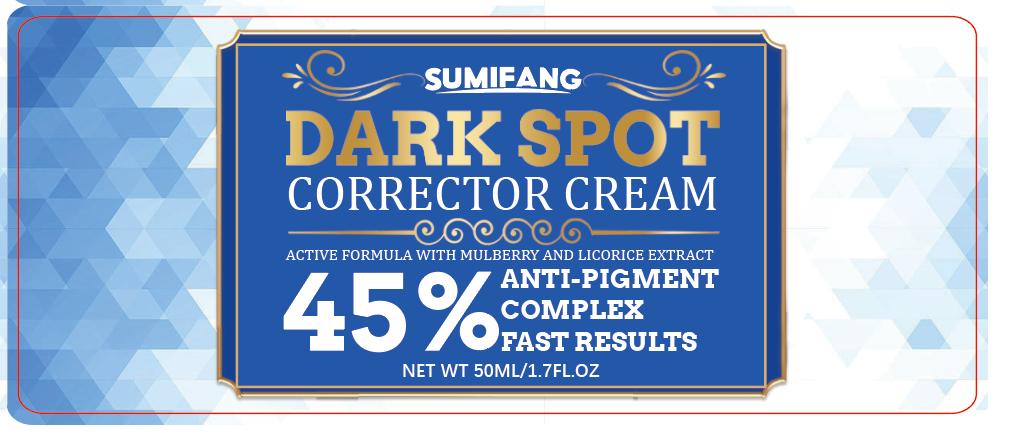 DRUG LABEL: Face cream
NDC: 84025-067 | Form: LOTION/SHAMPOO
Manufacturer: Guangzhou Yanxi Biotechnology Co., Ltd
Category: otc | Type: HUMAN OTC DRUG LABEL
Date: 20240712

ACTIVE INGREDIENTS: CETEARYL OLIVATE 2 g/50 mL; NIACINAMIDE 4 g/50 mL
INACTIVE INGREDIENTS: WATER

DOSAGE AND ADMINISTRATION

use as a normal facial cream

WARNINGS

Keep out of Children

INACTIVE INGREDIENT

Aqua

INDICATIONS AND USAGE

For daily facial care

Keep out of Children

PURPOSE

dark spot corrector cream
anti-pigment